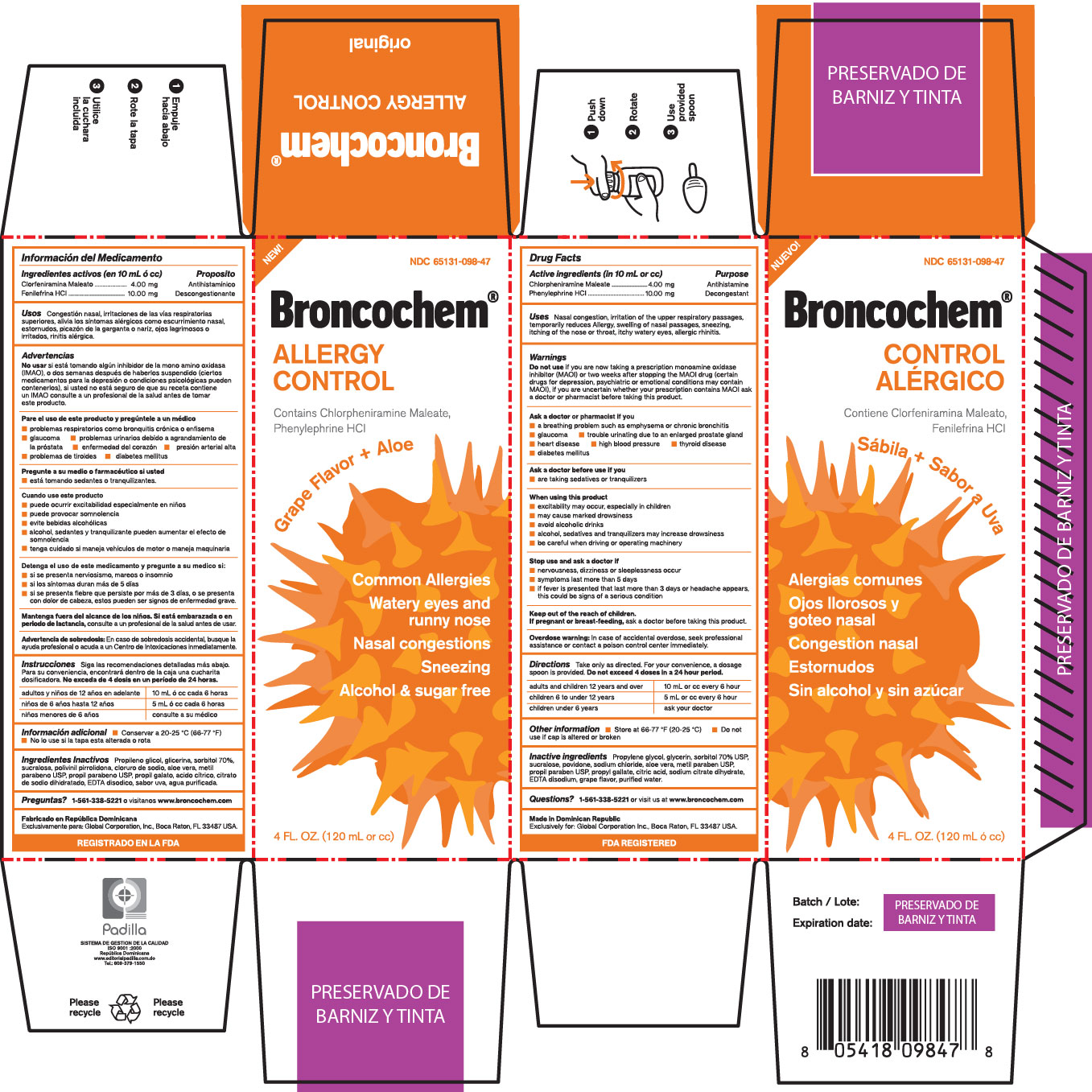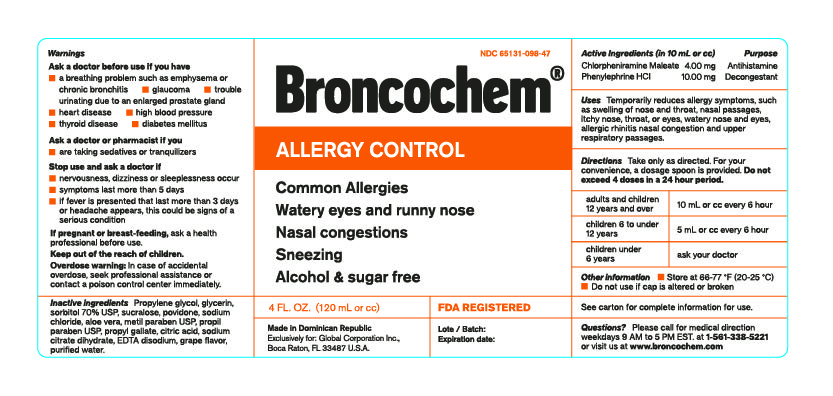 DRUG LABEL: BRONCOCHEM
NDC: 65131-098 | Form: SYRUP
Manufacturer: LABORATORIO MAGNACHEM INTERNATIONAL SRL
Category: otc | Type: HUMAN OTC DRUG LABEL
Date: 20170314

ACTIVE INGREDIENTS: CHLORPHENIRAMINE MALEATE 4 mg/10 mL; PHENYLEPHRINE HYDROCHLORIDE 10 mg/10 mL
INACTIVE INGREDIENTS: PROPYLENE GLYCOL 1.2 mL/10 mL; GLYCERIN 2 mL/10 mL; SORBITOL 2 mL/10 mL; SUCRALOSE 7.5 mg/10 mL; POVIDONE K90 100 mg/10 mL; SODIUM CHLORIDE 6.25 mg/10 mL; ALOE VERA LEAF 4 mg/10 mL; METHYLPARABEN 10 mg/10 mL; PROPYLPARABEN 1.5 mg/10 mL; PROPYL GALLATE 1 mg/10 mL; CITRIC ACID ACETATE 20 mg/10 mL; TRISODIUM CITRATE DIHYDRATE 40 mg/10 mL; EDETATE SODIUM 0.9 mg/10 mL; GRAPEFRUIT 0.0048 mL/10 mL; WATER 10 mL/10 mL

BRONCOCHEM ALLERGY CONTROL

Warnings

If you are now taking a prescription monoamine oxidase inhibitor (MAOI) or two weeks after stopping the MAOI drug (certain drugs for depression, psychiatric or emotional conditions may contain MAOI) If you are uncertain whether your prescription contains MAOI ask a doctor or oharmacist before taking this product.

Uses

Nasal congestion, irritation of the upper respiratory passages, temporarily reduces allergy, swelling of nasal passages, sneezing, itching of the nose or throat, itchy watery eyes, allergic rhinitis.

Active ingredients (in 10 mL or cc)

Chlorpheniramine Maleate.......4.00mg (antihistamine)

Phenylephrine HCl..................5.00mg (Decongestant)

Ask a doctor or Pharmacist if you

Are taking sedatives or tranquilizers

When Using this Product

Excitability may occur, especially in children.

May cause marked drowsiness

Avoid alcoholic drinks

Alcohol, sedatives and tranquilizers may increase drowsiness

Be careful when driving or operating machinery

Stop Use and Ask a Doctor If

Nervousness, dizziness or sleeplessness occur.

Symptoms last more than five days.

If fever is presented that last more than 3 days or headache appers, this could be signs of a serious condition.

Keep Out of the Reach of children

If pregnant or breast-feeding, ask a doctor before taking this product.

Overdose warning

In case of accidental overdose, seek professional assistance or contact a poison control center inmediately.

Directions

Take only as directed, for your convenience a dosage spoon is provided. Do not exceed 4 doses in a 24-hour period.

Adults and Children from 12 years above 10mL or cc every 6 hours.

Children from 6 to 12 years 5mL or cc every 6 hours.

Children under 6 years, ask your doctor.

Other Information

Store at 66-77

Inactive Ingredients

Propylene glycol, Glicerin, Sorbitol 70% USP, sucralose, Povidone, Sodium chloride, Aloe Vera, Metil paraben USP, Propil paraben USP, Propyl gallate, Citric acid, Sodium citrate dihydrate, EDTA disodium, Grape flavor, Purified water.

Questions

1-561-338-5221 or visit us at www.broncochem.com

Made in Dominican Republic by Laboratorio Magnachem International SRL to Global Corporation Inc. Boca Raton, Fl 33487